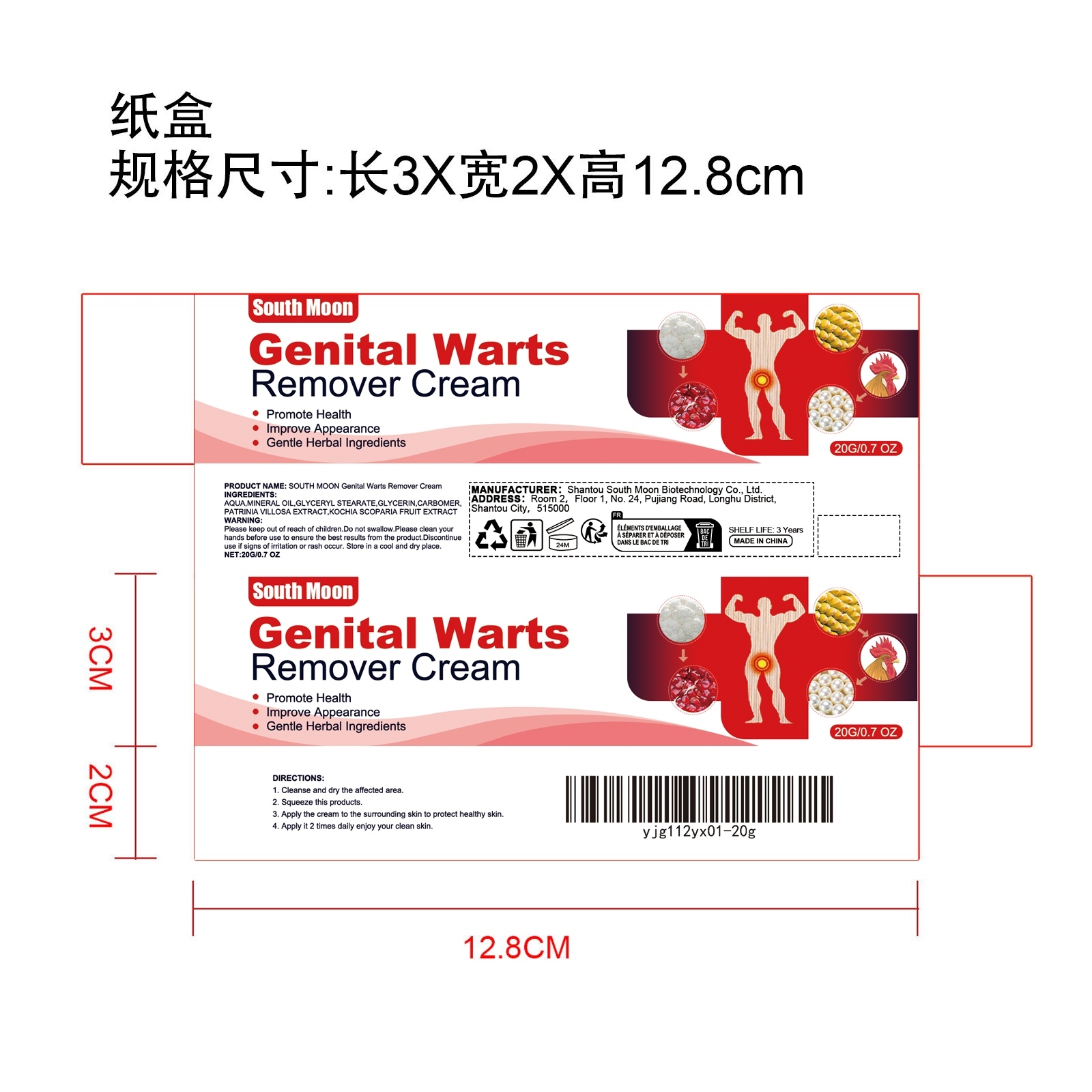 DRUG LABEL: SOUTH MOON Genital Warts Remover Cream
NDC: 84983-010 | Form: CREAM
Manufacturer: Shantou South Moon Biotechnology Co., Ltd.
Category: otc | Type: HUMAN OTC DRUG LABEL
Date: 20251127

ACTIVE INGREDIENTS: BASSIA SCOPARIA FRUIT 0.004 mg/20 mg; PATRINIA VILLOSA WHOLE 0.004 mg/20 mg
INACTIVE INGREDIENTS: GLYCERYL STEARATE 0.4 mg/20 mg; AQUA 17.152 mg/20 mg; CARBOMER 0.04 mg/20 mg; MINERAL OIL 2 mg/20 mg; GLYCERIN 0.4 mg/20 mg

ACTIVE INGREDIENT

PATRINIA VILLOSA EXTRACT、BASSIA SCOPARIA FRUIT

PURPOSE

/

WHEN USING

1. Cleanse and dry the affected area.

2. Squeeze this products.

3. Apply the cream to the surrounding skin to protect healthy skin.

4. Apply it 2 times daily enjoy your clean skin.

WARNINGS

Please keep out of reach of children. Do not swallow.Please clean your hands before use to ensure the best results from the product. Discontinue use if signs of irritation or rash occur. Store in a cool and dry place.

DO NOT USE

Discontinue use if signs of irritation or rash occur.

STOP USE

Discontinue use if signs of irritation or rash occur.

KEEP OUT OF REACH OF CHILDREN

Please keep out of reach of children. Do not swallow.

STORAGE AND HANDLING

Store in a cool and dry place.

INACTIVE INGREDIENT

AQUA、MINERAL OIL、GLYCERYL STEARATE、CARBOMER